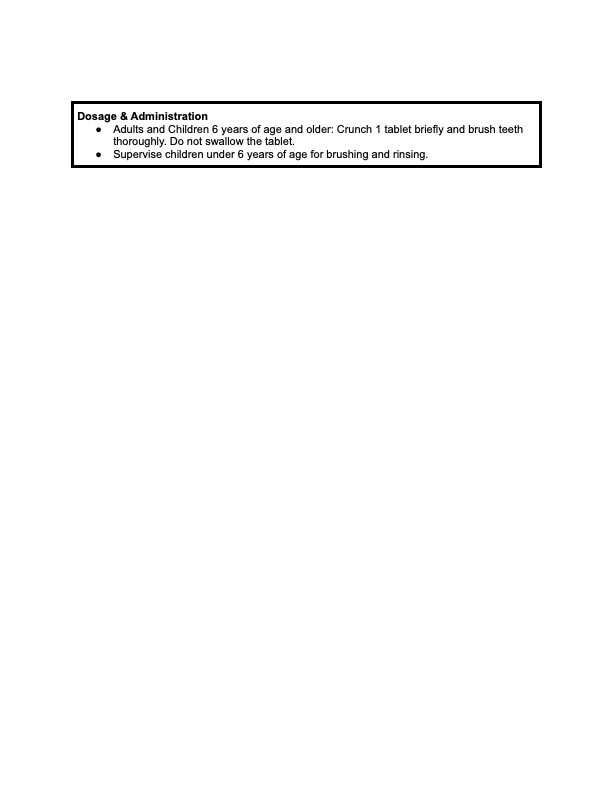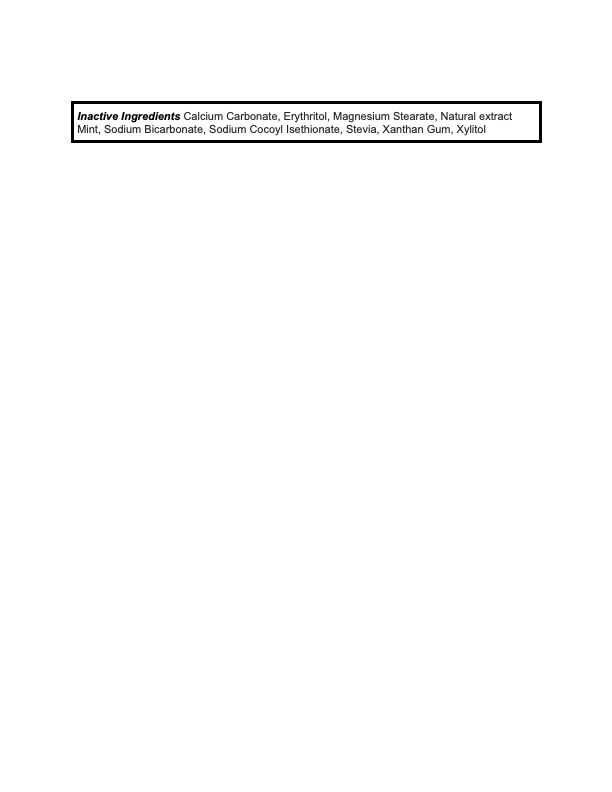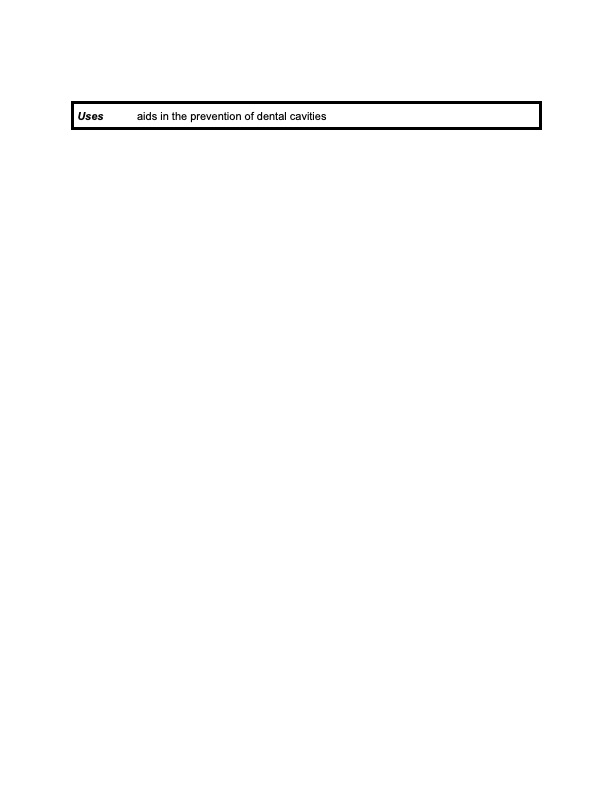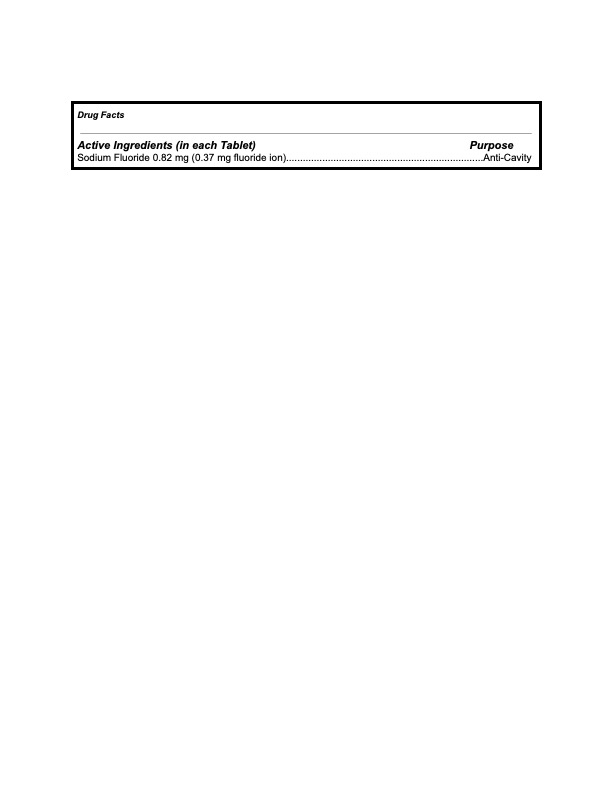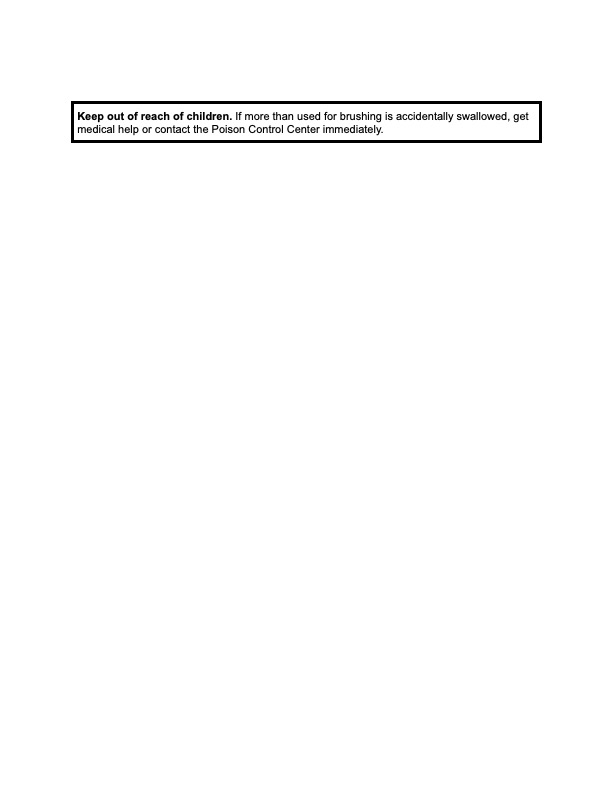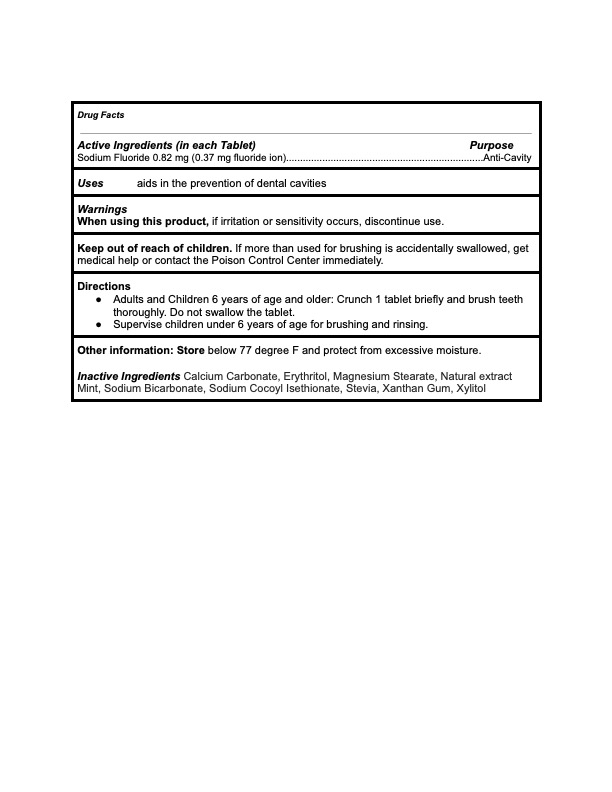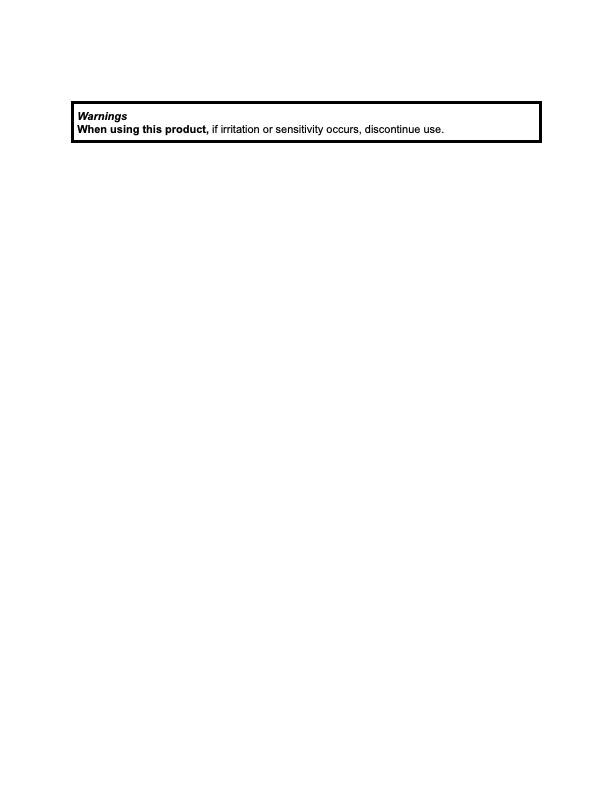 DRUG LABEL: KAYLAAN
NDC: 82091-112 | Form: TABLET, CHEWABLE
Manufacturer: Kaylaan LLC
Category: otc | Type: HUMAN OTC DRUG LABEL
Date: 20210907

ACTIVE INGREDIENTS: SODIUM FLUORIDE 0.37 mg/440 mg
INACTIVE INGREDIENTS: STEVIA LEAF; ERYTHRITOL; SODIUM COCOYL ISETHIONATE; XANTHAN GUM; MINT; CALCIUM CARBONATE; SODIUM BICARBONATE; MAGNESIUM STEARATE; XYLITOL

Kaylaan Mint Toothpaste Tablet